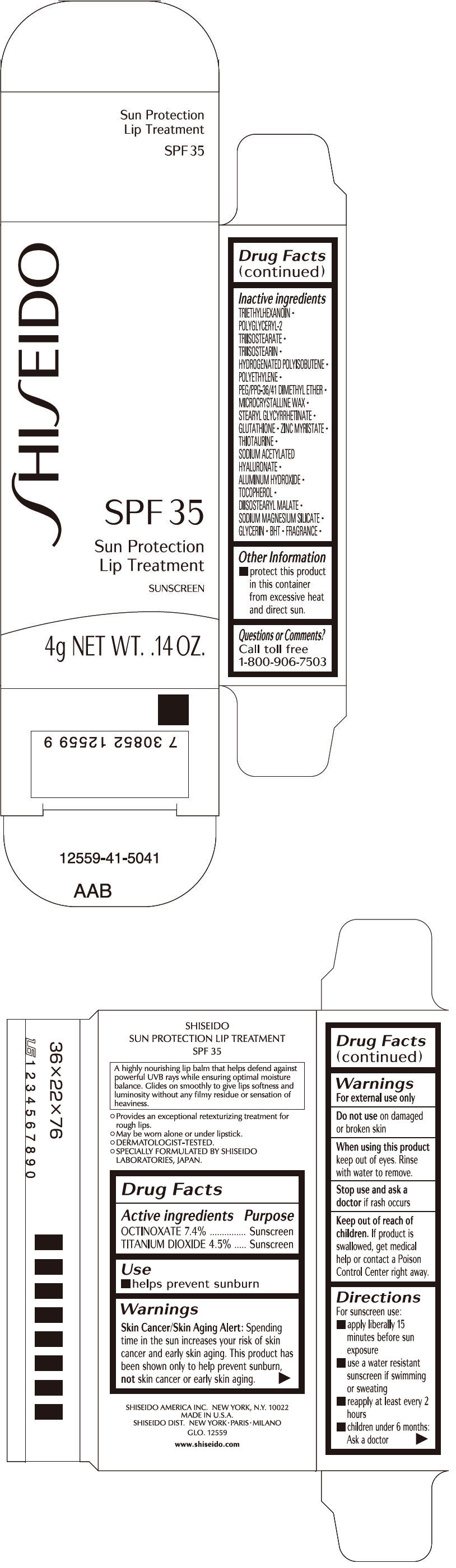 DRUG LABEL: SHISEIDO SUN PROTECTION LIP TREATMENT
NDC: 52686-642 | Form: LIPSTICK
Manufacturer: SHISEIDO AMERICA INC.
Category: otc | Type: HUMAN OTC DRUG LABEL
Date: 20181213

ACTIVE INGREDIENTS: OCTINOXATE 296 mg/4 g; TITANIUM DIOXIDE 180 mg/4 g
INACTIVE INGREDIENTS: TRIETHYLHEXANOIN; TRIISOSTEARIN; HYDROGENATED POLYBUTENE (1300 MW); HIGH DENSITY POLYETHYLENE; PEG/PPG-36/41 DIMETHYL ETHER; MICROCRYSTALLINE WAX; STEARYL GLYCYRRHETINATE; GLUTATHIONE; ZINC MYRISTATE; THIOTAURINE; ALUMINUM HYDROXIDE; .ALPHA.-TOCOPHEROL; DIISOSTEARYL MALATE; GLYCERIN; BUTYLATED HYDROXYTOLUENE

SHISEIDO SUN PROTECTION LIP TREATMENT

Drug Facts

ACTIVE INGREDIENT

ACTIVE INGREDIENTS: | Purpose
OCTINOXATE 7.4% | Sunscreen
TITANIUM DIOXIDE 4.5% | Sunscreen

Use

- helps prevent sunburn

Warnings

Skin Cancer/Skin Aging Alert

Spending time in the sun increases your risk of skin cancer and early skin aging. This product has been shown only to prevent sunburn, not skin cancer or early skin aging.

For external use only

Do not use on damaged or broken skin

When using this product keep out of eyes. Rinse with water to remove.

Stop use and ask a doctor if rash occurs

Keep out of reach of children. If product is swallowed, get medical help or contact a Poison Control Center right away.

Directions

For sunscreen use:

- apply liberally 15 minutes before sun exposure
- use a water resistant sunscreen if swimming or sweating
- reapply at least every 2 hours
- children under 6 months: Ask a doctor

Inactive Ingredients

TRIETHYLHEXANOIN, POLYGLYCERYL-2 TRIISOSTEARATE, TRIISOSTEARIN, HYDROGENATED POLYISOBUTENE, POLYETHYLENE, PEG/PPG-36/41 DIMETHYL ETHER, MICROCRYSTALLINE WAX, STEARYL GLYCYRRHETINATE, GLUTATHIONE, ZINC MYRISTATE, THIOTAURINE, SODIUM ACETYLATED HYALURONATE, ALUMINUM HYDROXIDE, TOCOPHEROL, DIISOSTEARYL MALATE, SODIUM MAGNESIUM SILICATE, GLYCERIN, BHT, FRAGRANCE,

Other information

- protect this product in this container from excessive heat and direct sun.

Questions or comments?

Call toll free 1-800-906-7503

PRINCIPAL DISPLAY PANEL - 4g Cartridge Carton

SHI SEIDO

SPF 35

Sun Protection
Lip Treatment

SUNSCREEN

4g NET WT. .14 OZ.